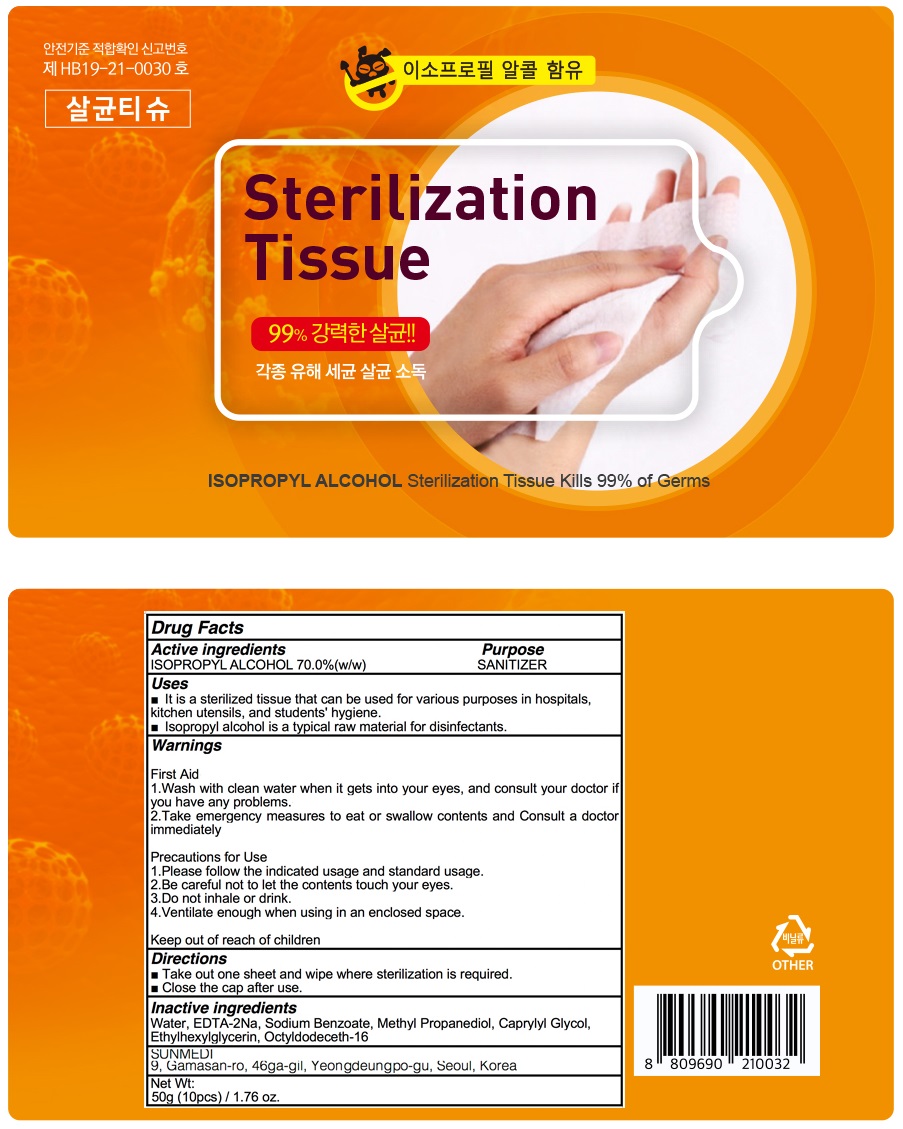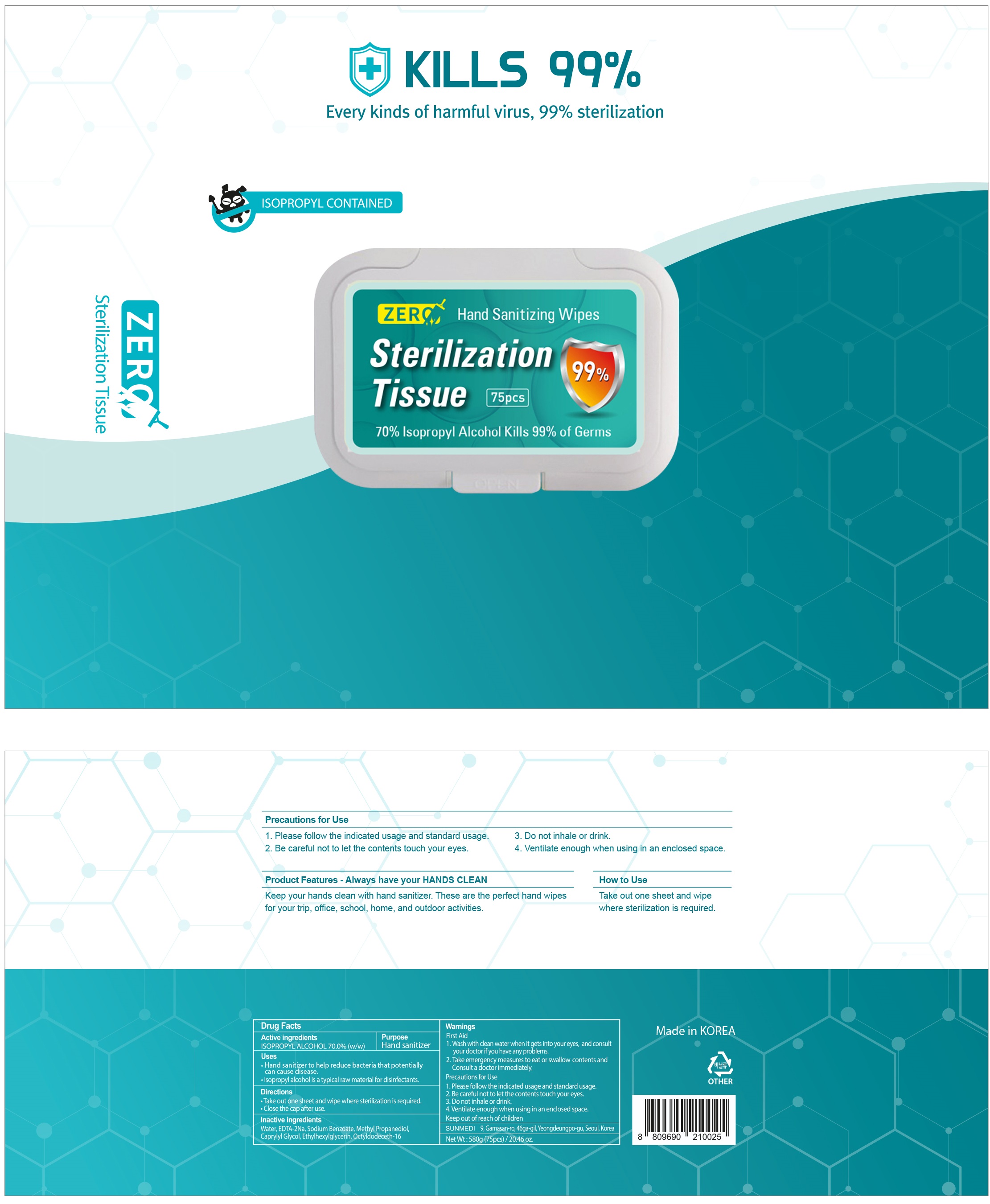 DRUG LABEL: Gyun e zero sterilization tissue
NDC: 75578-020 | Form: LIQUID
Manufacturer: Sunmedi
Category: otc | Type: HUMAN OTC DRUG LABEL
Date: 20250810

ACTIVE INGREDIENTS: ISOPROPYL ALCOHOL 70 g/100 g
INACTIVE INGREDIENTS: WATER; SODIUM BENZOATE; METHYLPROPANEDIOL; CAPRYLYL GLYCOL; ETHYLHEXYLGLYCERIN; OCTYLDODECETH-16

Active Ingredient

ISOPROPYL ALCOHOL 70.0%(w/w)

INACTIVE INGREDIENTS

Water, EDTA-2Na, Sodium Benzoate, Methyl Propanediol, Caprylyl Glycol, Ethylhexylglycerin, Octyldodeceth-16

Purpose

Hand Sanitizer

Warnings

First Aid
1. Wash with clean water when it gets into your eyes, and consult your doctor if you have any problems.
2. Take emergency measures to eat or swallow contents and Consult a doctor immediately.

Precautions for Use
1. Please follow the indicated usage and standard usage.
2. Be careful not to let the contents touch your eyes.
3. Do not inhale or drink.
4. Ventilate enough when using in an enclosed space.

KEEP OUT OF REACH OF CHILDREN

Uses

■ Hand sanitizer to help reduce bacteria that potentially can cause disease.

■ Isopropyl alcohol is a typical raw material for disinfectants.

Directions

■ Take out one sheet and wipe where sterilization is required.

■ Close the cap after use.